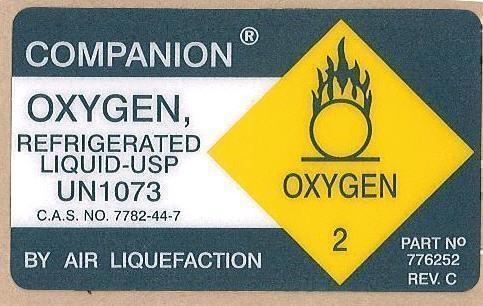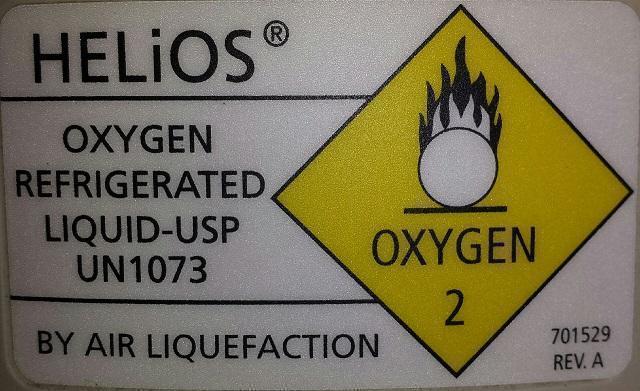 DRUG LABEL: Liquid Oxygen
NDC: 60919-1073 | Form: GAS
Manufacturer: Hospice Express, Inc.
Category: prescription | Type: HUMAN PRESCRIPTION DRUG LABEL
Date: 20131205

ACTIVE INGREDIENTS: OXYGEN 995 mL/1 L

PACKAGE LABEL

COMPANION®
OXYGEN,
REFRIGERATED
LIQUID-USP
UN1073
C.A.S. NO. 7782-44-7

BY AIR LIQUEFACTION

PART No
776252
REV. C

PACKAGE LABEL

HELiOS®

OXYGEN

REFRIGERATED

LIQUID-USP

UN1073

BY AIR LIQUEFACTION

701529

REV. A